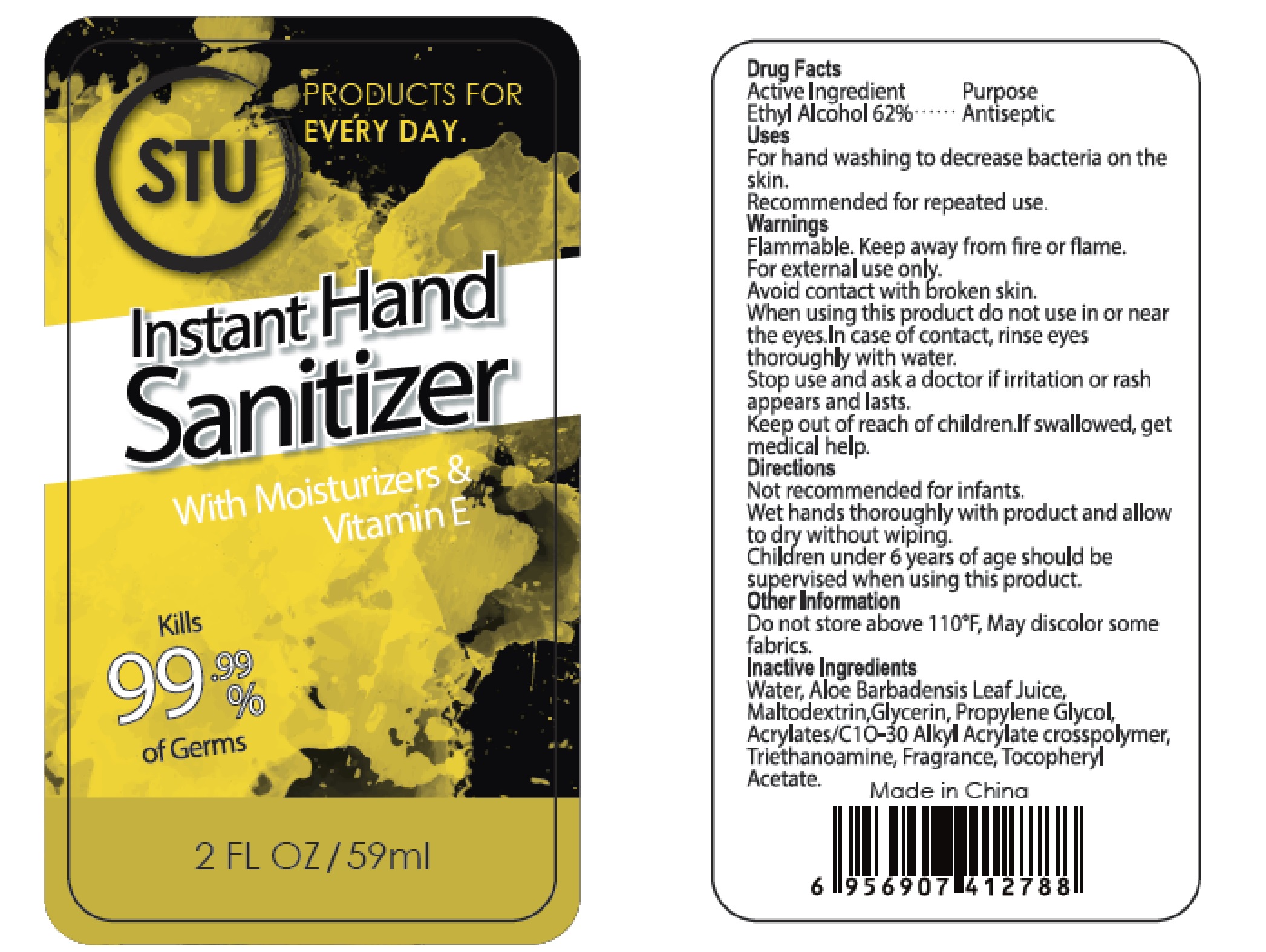 DRUG LABEL: Hand Sanitizer
NDC: 78602-002 | Form: GEL
Manufacturer: Three Square Market, Inc
Category: otc | Type: HUMAN OTC DRUG LABEL
Date: 20200601

ACTIVE INGREDIENTS: ALCOHOL 62 mL/100 mL
INACTIVE INGREDIENTS: MALTODEXTRIN; PROPYLENE GLYCOL; WATER; ALOE VERA LEAF; GLYCERIN; CARBOMER INTERPOLYMER TYPE A (55000 CPS); .ALPHA.-TOCOPHEROL ACETATE; TROLAMINE

Active Ingredient
Ethyl Alcohol 62%

Purpose
Antiseptic

Uses

For hand washing to decrease bacteria on the skin.

Recommended for repeated use.

Warnings

Flammable. Keep away from fire or flame.

For external use only.

Avoid contact with broken skin.

When using this product do not use in or near the eyes.In case of contact, rinse eyes thoroughly with

water.

Stop use and ask a doctor if irritation or rash appears and lasts.

Keep out of reach of children. If swallowed, get medical help.

Directions

Not recommended for infants.

Wet hands thoroughly with product and allow to dry without wiping.

Children under 6 years of age should be supervised when using this product.

Other Information

Do not store above 110°F. May discolor some fabrics.

Inactive Ingredients

Water, Aloe Barbadensis Leaf Juice, Maltodextrin, Glycerin, Propylene Glycol, Acrylates/C10-30 Alkyl Acrylate crosspolymer, Triethanoamine, Fragrance, Tocopheryl Acetate.